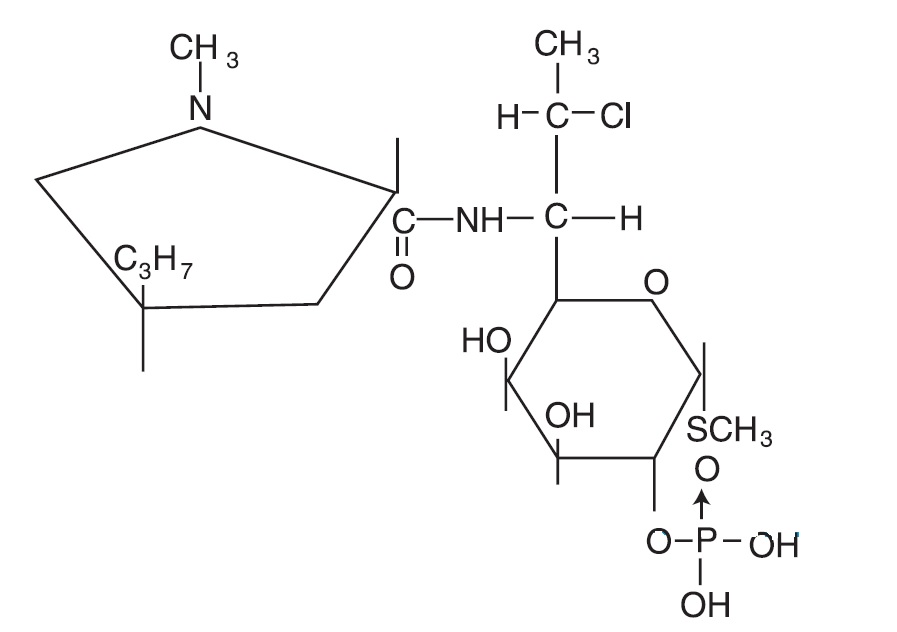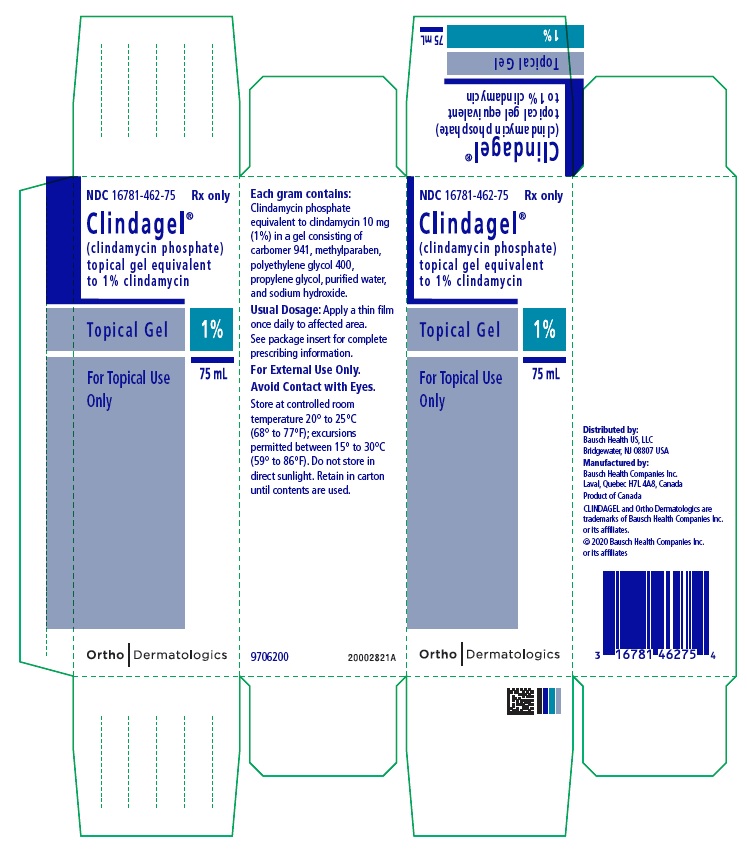 DRUG LABEL: Clindagel
NDC: 16781-462 | Form: GEL
Manufacturer: Bausch Health US, LLC
Category: prescription | Type: HUMAN PRESCRIPTION DRUG LABEL
Date: 20200101

ACTIVE INGREDIENTS: CLINDAMYCIN PHOSPHATE 10 mg/1 mL
INACTIVE INGREDIENTS: METHYLPARABEN; POLYETHYLENE GLYCOL 400; PROPYLENE GLYCOL; SODIUM HYDROXIDE; WATER; CARBOMER HOMOPOLYMER TYPE A (ALLYL PENTAERYTHRITOL CROSSLINKED)

Clindagel®
(clindamycin phosphate)
topical gel, 1%
For Topical Use Only

DESCRIPTION

CLINDAGEL (clindamycin phosphate) topical gel, 1%, a topical antibiotic, contains clindamycin phosphate, USP, at a concentration equivalent to 10 mg clindamycin per gram in a gel vehicle consisting of carbomer 941, methylparaben, polyethylene glycol 400, propylene glycol, purified water, and sodium hydroxide. Chemically, clindamycin phosphate is a water-soluble ester of the semi-synthetic antibiotic produced by a 7 (S)-chlorosubstitution of the 7 (R)-hydroxyl group of the parent antibiotic, lincomycin, and has the structural formula represented below:

The chemical name for clindamycin phosphate is methyl 7-chloro-6,7,8-trideoxy-6-(1-methyl-trans-4-propyl-L-2-pyrrolidinecarboxamido)-1-thio-L-threo-α-D-galacto-octopyranoside 2-(dihydrogen phosphate).

CLINICAL PHARMACOLOGY

Pharmacokinetics: In an open-label, parallel group study of 24 patients with acne vulgaris, once-daily topical administration of approximately 3 to 12 grams/day of CLINDAGEL for 5 days resulted in peak plasma clindamycin concentrations that were less than 5.5 ng/mL.

Following multiple applications of CLINDAGEL less than 0.04% of the total dose was excreted in the urine.

Microbiology: Although clindamycin phosphate is inactive in vitro, rapid in vitro hydrolysis converts this compound to clindamycin, which has antibacterial activity. Clindamycin inhibits bacteria protein synthesis at the ribosomal level by binding to the 50S ribosomal subunit and affecting the process of peptide chain initiation. In vitro studies indicated that clindamycin inhibited all tested Propionibacterium acnes cultures at a minimum inhibitory concentration (MIC) of 0.4 mcg/mL. Cross-resistance has been demonstrated between clindamycin and erythromycin.

CLINICAL STUDIES

In one 12-week multicenter, randomized, evaluator-blind, vehicle-controlled, parallel comparison clinical trial in which patients used CLINDAGEL (clindamycin phosphate topical gel, 1%) once daily or the vehicle gel once daily, in the treatment of acne vulgaris of mild to moderate severity, CLINDAGEL applied once daily was more effective than the vehicle applied once daily. The mean percent reductions in lesion counts at the end of treatment in this study are shown in the following table:

Lesions | CLINDAGEL QD N=162 | Vehicle Gel QD N=82
Inflammatory | 51% | 40% [P<0.05]
Noninflammatory | 25% | 12%
Total | 38% | 27%

There was a trend in the investigator’s global assessment of the results, which favored CLINDAGEL QD over the vehicle QD.

In a contact sensitization study, four of the 200 subjects appeared to develop suggestive evidence of allergic contact sensitization to CLINDAGEL. There was no signal for contact sensitization in the clinical trials under normal use conditions.

INDICATIONS AND USAGE

CLINDAGEL is indicated for topical application in the treatment of acne vulgaris. In view of the potential for diarrhea, bloody diarrhea, and pseudomembranous colitis, the physician should consider whether other agents are more appropriate (see CONTRAINDICATIONS, WARNINGS, and ADVERSE REACTIONS).

CONTRAINDICATIONS

CLINDAGEL is contraindicated in individuals with a history of hypersensitivity to preparations containing clindamycin or lincomycin, a history of regional enteritis or ulcerative colitis, or a history of antibiotic-associated colitis.

WARNINGS

Orally and parenterally administered clindamycin has been associated with severe colitis, which may result in patient death. Use of the topical formulation of clindamycin results in absorption of the antibiotic from the skin surface. Diarrhea, bloody diarrhea, and colitis (including pseudomembranous colitis) have been reported with the use of topical and systemic clindamycin.

Studies indicate a toxin(s) produced by Clostridia is one primary cause of antibiotic-associated colitis. The colitis is usually characterized by severe persistent diarrhea and severe abdominal cramps and may be associated with the passage of blood and mucus. Endoscopic examination may reveal pseudomembranous colitis. Stool culture for Clostridium difficile and stool assay for C. difficile toxin may be helpful diagnostically.

When significant diarrhea occurs, the drug should be discontinued. Large bowel endoscopy should be considered to establish a definitive diagnosis in cases of severe diarrhea. Antiperistaltic agents, such as opiates and diphenoxylate with atropine, may prolong and/or worsen the condition.

Diarrhea, colitis, and pseudomembranous colitis have been observed to begin up to several weeks following cessation of oral and parenteral therapy with clindamycin.

PRECAUTIONS

General: CLINDAGEL should be prescribed with caution in atopic individuals.

Drug Interactions: Clindamycin has been shown to have neuromuscular blocking properties that may enhance the action of other neuromuscular blocking agents. Therefore, it should be used with caution in patients receiving such agents.

Carcinogenesis, Mutagenesis, Impairment of Fertility:

The carcinogenicity of a 1% clindamycin phosphate gel similar to CLINDAGEL was evaluated by daily application to mice for 2 years. The daily doses used in this study were approximately 3 and 15 times higher than the human dose of clindamycin phosphate from 5 mL of CLINDAGEL, assuming complete absorption and based on a body surface area comparison. No significant increase in tumors was noted in the treated animals.

A 1% clindamycin phosphate gel similar to CLINDAGEL caused a statistically significant shortening of the median time to tumor onset in a study in hairless mice in which tumors were induced by exposure to simulated sunlight.

Genotoxicity tests performed included a rat micronucleus test and an Ames Salmonella reversion test. Both tests were negative. Reproduction studies in rats using oral doses of clindamycin hydrochloride and clindamycin palmitate hydrochloride have revealed no evidence of impaired fertility.

Pregnancy:

Teratogenic Effects:

Reproduction studies have been performed in rats and mice using subcutaneous and oral doses of clindamycin phosphate, clindamycin hydrochloride, and clindamycin palmitate hydrochloride. These studies revealed no evidence of fetal harm. The highest dose used in the rat and mouse teratogenicity studies was equivalent to a clindamycin phosphate dose of 432 mg/kg. For a rat, this dose is 84-fold higher and for a mouse, 42-fold higher than the anticipated human dose of clindamycin phosphate from CLINDAGEL based on a mg/m^2 comparison. There are, however, no adequate and well-controlled studies in pregnant women. Because animal reproduction studies are not always predictive of human response, this drug should be used during pregnancy only if clearly needed.

Nursing Mothers:

It is not known whether clindamycin is excreted in human milk following use of CLINDAGEL. However, orally and parenterally administered clindamycin has been reported to appear in breast milk. Because of the potential for serious adverse reactions in nursing infants, a decision should be made whether to discontinue nursing or to discontinue the drug, taking into account the importance of the drug to the mother.

Pediatric Use:

Safety and effectiveness in children under the age of 12 have not been established.

Geriatric Use:

The clinical study with CLINDAGEL did not include sufficient numbers of patients aged 65 and over to determine if they respond differently than younger patients.

ADVERSE REACTIONS

In the one well-controlled clinical study comparing CLINDAGEL and its vehicle, the incidence of skin and appendages adverse events occurring in ≥1% of the patients in either group is presented in the following table:

 | Number (%) of Patients
Body System/Adverse Event | CLINDAGEL QD N=168 | Vehicle Gel QD N=84
Skin and Appendages Disorders
Dermatitis | 0 (0.0) | 1 (1.2)
Dermatitis contact | 0 (0.0) | 1 (1.2)
Dermatitis fungal | 0 (0.0) | 1 (1.2)
Folliculitis | 0 (0.0) | 1 (1.2)
Photosensitivity reaction | 0 (0.0) | 1 (1.2)
Pruritus | 1 (0.6) | 1 (1.2)
Rash erythematous | 0 (0.0) | 0 (0.0)
Skin dry | 0 (0.0) | 0 (0.0)
Peeling | 1 (0.6) | 0 (0.0)

Orally and parenterally administered clindamycin has been associated with severe colitis, which may end fatally.

Cases of diarrhea, bloody diarrhea, and colitis (including pseudomembranous colitis) have been reported as adverse reactions in patients treated with oral and parenteral formulations of clindamycin and rarely with topical clindamycin (see WARNINGS). Abdominal pain and gastrointestinal disturbances, as well as gram-negative folliculitis, have also been reported in association with the use of topical formulations of clindamycin.

To report SUSPECTED ADVERSE REACTIONS, contact Bausch Health US, LLC at 1-800-321-4576 or FDA at 1-800-FDA-1088 or www.fda.gov/medwatch.

OVERDOSAGE

Topically applied CLINDAGEL may be absorbed in sufficient amounts to produce systemic effects (see WARNINGS).

DOSAGE AND ADMINISTRATION

Apply a thin film of CLINDAGEL once daily to the skin where acne lesions appear. Use enough to cover the entire affected area lightly.

Keep container tightly closed.

HOW SUPPLIED

CLINDAGEL containing clindamycin phosphate equivalent to 10 mg clindamycin per gram is available in the following size:

75 mL bottle - NDC 16781-462-75

Store at controlled room temperature 20°to 25°C (68° to 77°F); excursions permitted between 15° to 30°C (59° to 86°F). Do not store in direct sunlight.

Retain in carton until contents are used.

Distributed by:
Bausch Health US, LLC
Bridgewater, NJ 08807 USA

Manufactured by:
Bausch Health Companies Inc.
Laval, Quebec H7L 4A8, Canada

CLINDAGEL is a trademark of
Bausch Health Companies Inc. or its affiliates.

© 2020 Bausch Health Companies Inc. or its affiliates

9706100

Rev. 01/20

Package/Label Display Panel Carton - CLINDAGEL

NDC 16781-462-75

Rx only

Clindagel®

(clindamycin phosphate)
topical gel equivalent
to 1% clindamycin

Topical Gel 1%

For Topical Use
Only

75 mL

Ortho Dermatologics